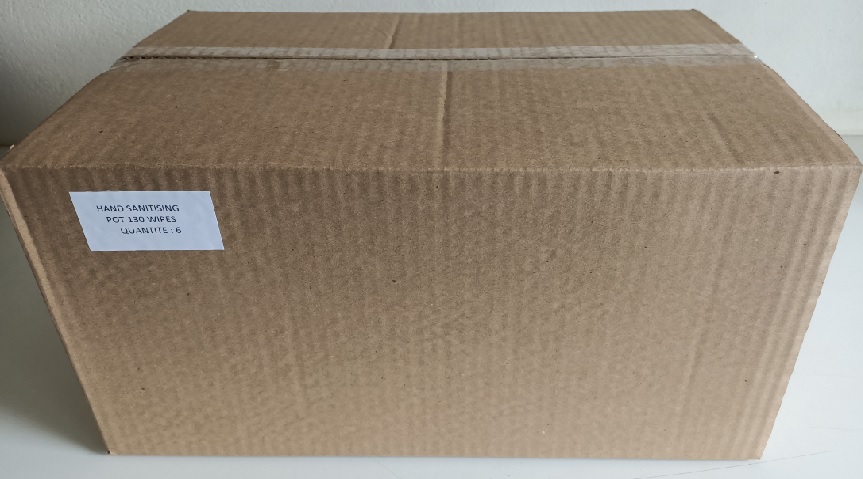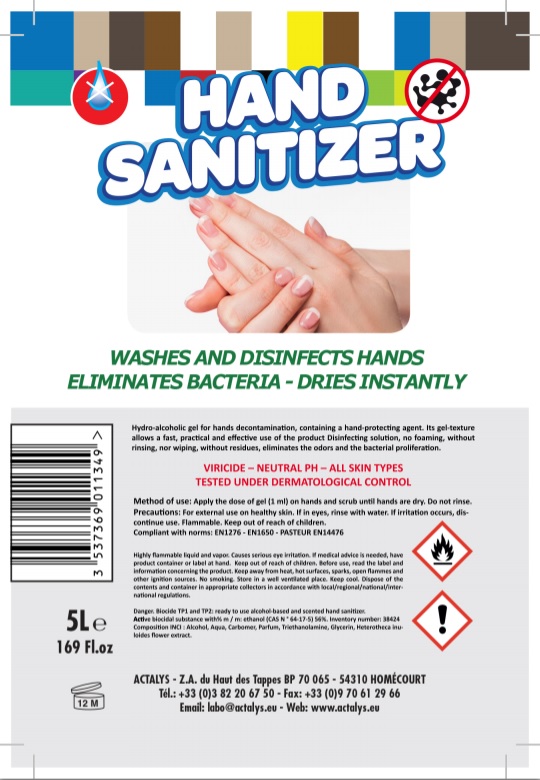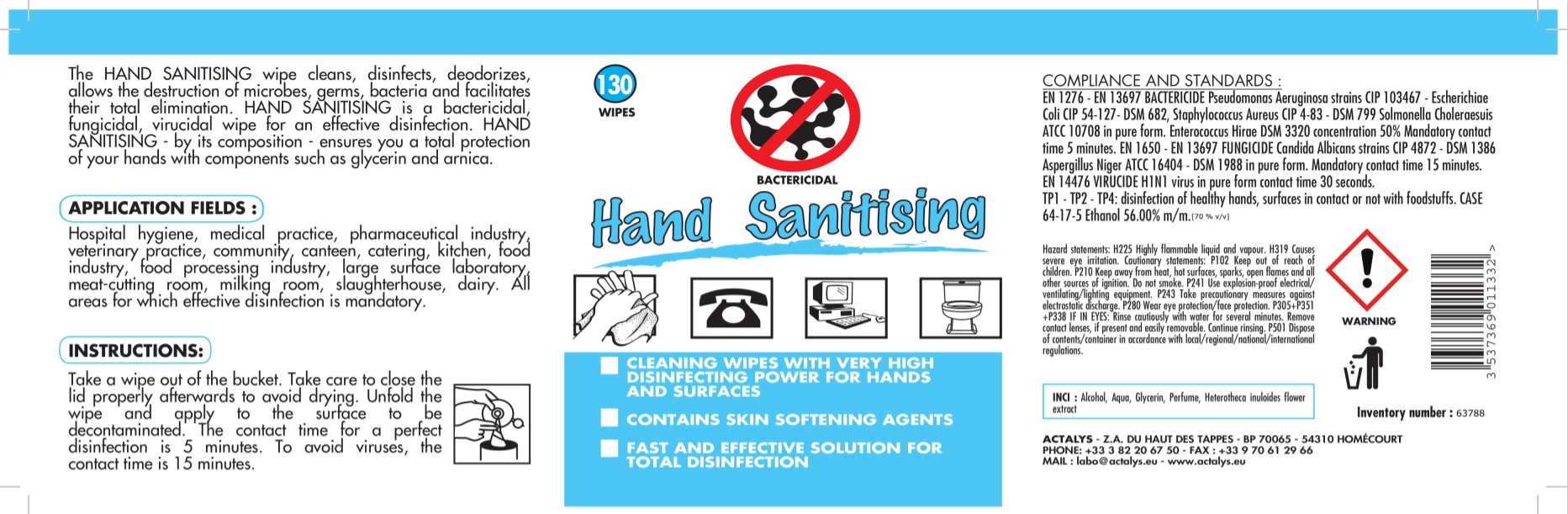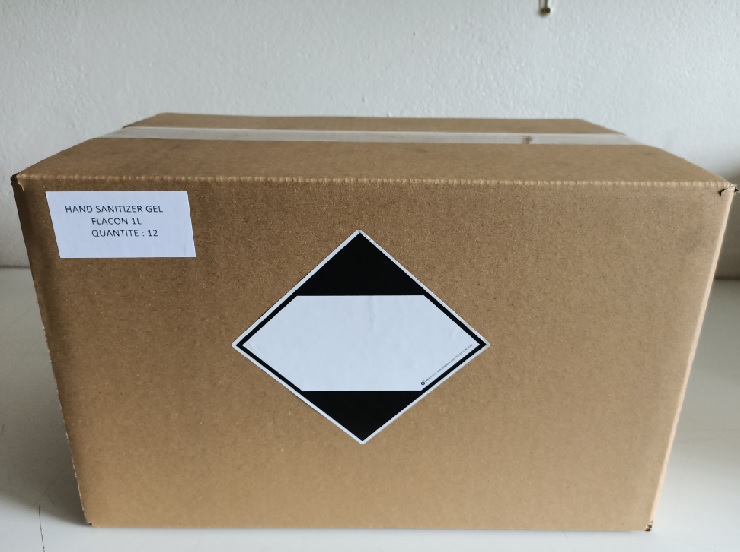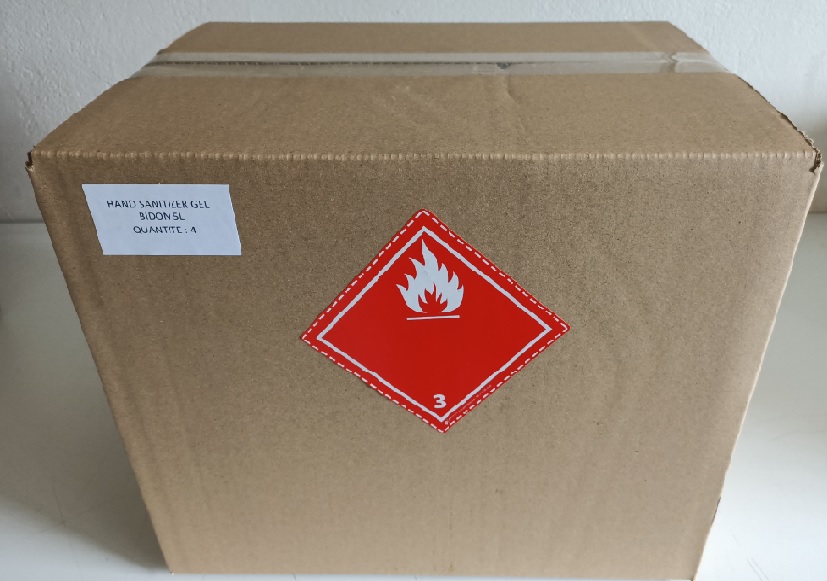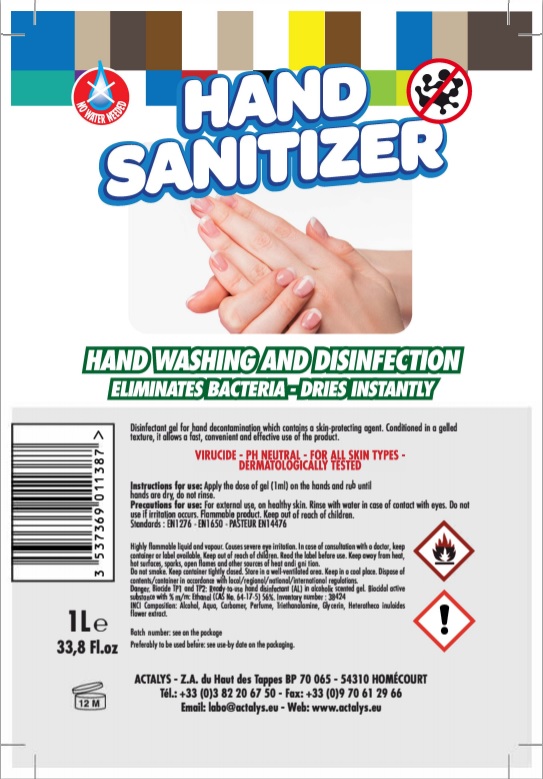 DRUG LABEL: Hand Sanitizer
NDC: 79032-202 | Form: GEL
Manufacturer: Actalys
Category: otc | Type: HUMAN OTC DRUG LABEL
Date: 20200708

ACTIVE INGREDIENTS: ALCOHOL 3.5 L/5 L
INACTIVE INGREDIENTS: HETEROTHECA INULOIDES FLOWER 0.1 L/5 L; TROLAMINE 0.01 L/5 L; CARBOMER HOMOPOLYMER, UNSPECIFIED TYPE 0.75 L/5 L; GLYCERIN 0.045 L/5 L; WATER 1.4185 L/5 L

Hand Sanitizer

5L NDC:79032-202-50

Inactive Ingredients

Water, Carbomer, Parfum, Triethanolamine, Glycerin, Heterotheca Inuloides Flower Extract

Active ingredient - Alcohol

Active Biocidal substance with % m/m: Ethanol (CAS N 64-175-) 56%

Purpose

Hydro-Alcoholic gel for hands decontamination, containing a hand-protecting agent. Its gel-texture allows a fast, practical, and effective use if the product disinfecting solution no foaming, without rinsing, nor wiping, without residues, eliminates the odors of bacterial proliferation.

Dosage

Apply the does of gel (1ml) on hands and scrub until hands are dry. Do not rinse

Usage

Apply the dose of gel (1 ml) on hands and scrub imtil the hands are dry. Do not rinse

Warnings - Flammable

Highly flammable liquid and vapor. Causes serious eye irritation. if medical advise is needed have product contianer or label at hand. Before use, read the label and information concerningthe product. Keep away from heat, hot surfaces, sparks, open flames, and other ignition sources. No smoking, store in well ventilated place. Keep cool. Dispose of the contents in apporopriate collectors in accordance with local/regional/national/international regulations.

Warnings - Biocide

Danger: Biocode TP1 and TP2: ready to use alcohol-based and scented hand sanitizer.

Active biocidal substance with % m/m: ethanol(CAS N 64-17-5) 56% Inventory number:38424

Keep out of reach of Children

Discontinue use

If irritation occurs, discontinue use

1L NDC 79032-213-11

Inactive Ingriedients

Water, Carbomer, Parfum, Triethanolamine, Glycerin, Heterotheca Inuloides Flower Extract

Active Ingredients

Active Biocidal substance with % m/m: Ethanol (CAS N 64-175-) 56%

Purpose

Hydro-Alcoholic gel for hands decontamination, containing a hand-protecting agent. Its gel-texture allows a fast, practical, and effective use if the product disinfecting solution no foaming, without rinsing, nor wiping, without residues, eliminates the odors of bacterial proliferation.

Dosage

Apply the does of gel (1ml) on hands and scrub until hands are dry. Do not rinse

Usage

Apply the dose of gel (1 ml) on hands and scrub imtil the hands are dry. Do not rinse

Warning - Flammable

Highly flammable liquid and vapor. Causes serious eye irritation. if medical advise is needed have product contianer or label at hand. Before use, read the label and information concerningthe product. Keep away from heat, hot surfaces, sparks, open flames, and other ignition sources. No smoking, store in well ventilated place. Keep cool. Dispose of the contents in apporopriate collectors in accordance with local/regional/national/international regulations.

Warning - Biocide

Danger: Biocode TP1 and TP2: ready to use alcohol-based and scented hand sanitizer.

Active biocidal substance with % m/m: ethanol(CAS N 64-17-5) 56% Inventory number:38424

Keep out of reach of Children

Discontinue Use

If irritation occurs, discontinue use

130 sheet package NDC:79032-209-13

Active Ingredient

Ethanol 56% m/m CASE 64-17-5

Inactive Ingredients

Water, Glycerin, Perume, Heterotheca inuloides flower extract, Thriethanolamine

Purpose

The Hand sanitizing wipe cleans, disinfects, deodorizes, allows the destruction of microbes, germs, bacteria, and facilitates their total elimination. Hand sanitizing is a bactericidal, fungicidal, virucidal wipe for an effective disinection. Hand sanitizing - by its composition - ensures you a total protection of your hands with components such as glycerin and arnica

Dosage

Take a wipe out of the bucket. Take care to close the lid properly afterwards to avoid drying. unfold the wipe and apply to the surface to be decontaminated. the contact time for a perfect disinfection is 5 minutes. to avoid viruses, the contact time is 15 minutes.

Usage

Take a wipe out of the bucket. Take care to close the lid properly afterwards to avoid drying. unfold the wipe and apply to the surface to be decontaminated. the contact time for a perfect disinfection is 5 minutes. to avoid viruses, the contact time is 15 minutes.

Warning - Flammable

Highly Flammable liquid and vapor. Keep away from heat, hot surfaces, sparks, open flames, and all other sources of ignition. Do not smoke. Use explosion-proof electrical/ventilating/lighting equipment. Take precautionary measures against electrostatic discharge.

Warning - Eye Irritant

Causes severe eye irritation. Wear eye protection/face protection.

If in eyes: rinse cautiously with water for several minutes. Remove contact lenses, if present and easily removable. Continue rinsing

Keep out of reach of Children

Disposal

Dispose of contents/container in accordance with local/regional/national/international regulations.